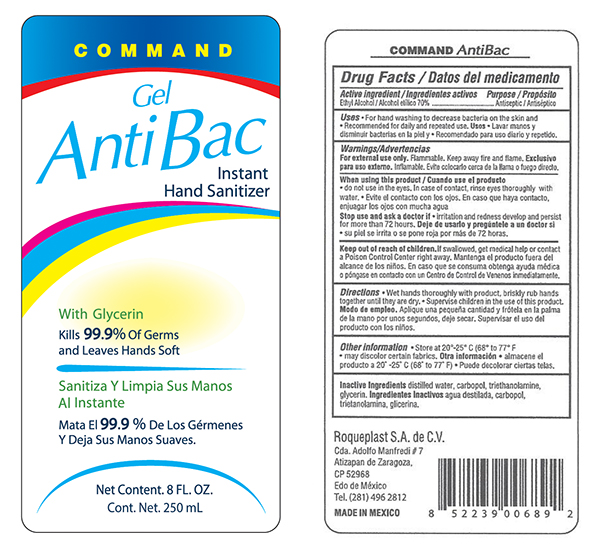 DRUG LABEL: Hand Sanitizer
NDC: 50058-100 | Form: GEL
Manufacturer: Roqueplast, S.A. de C.V.
Category: otc | Type: HUMAN OTC DRUG LABEL
Date: 20200116

ACTIVE INGREDIENTS: ALCOHOL 70 mL/100 mL
INACTIVE INGREDIENTS: GLYCERIN; TROLAMINE; WATER; CARBOMER HOMOPOLYMER, UNSPECIFIED TYPE

Command Hand Sanitizer

Active Ingredient

Alcohol 70%

Purpose

Antiseptic

Uses

■ For hand washing to decrease bacteria on the skin and ■ Recommended for daily and repeated use.

Warnings

For external use only. Flammable. Keep away from fire & flame

When using this product

■ do not use in the eyes. In case of contact, rinse eyes thoroughly with water

Stop use and ask a doctor if

■ irritation and redness develop and persist for more than 72 hours

Keep out of reach of children

If swallowed, get medical help or Poison Control Center right away.

Directions

■ Wet hands throughhly with product, briskly rub hands together until they are dry. ■ Supervise children in the use of this product.

Other information

■ Store below 105ºF

■ May discolor some fabrics

Other information

■ Store at 20º-25º C (68º to 72º F) ■ may discolor certain fabrics

Inactive Ingredients

distilled water, carbopol, triethanolamine, glycerin